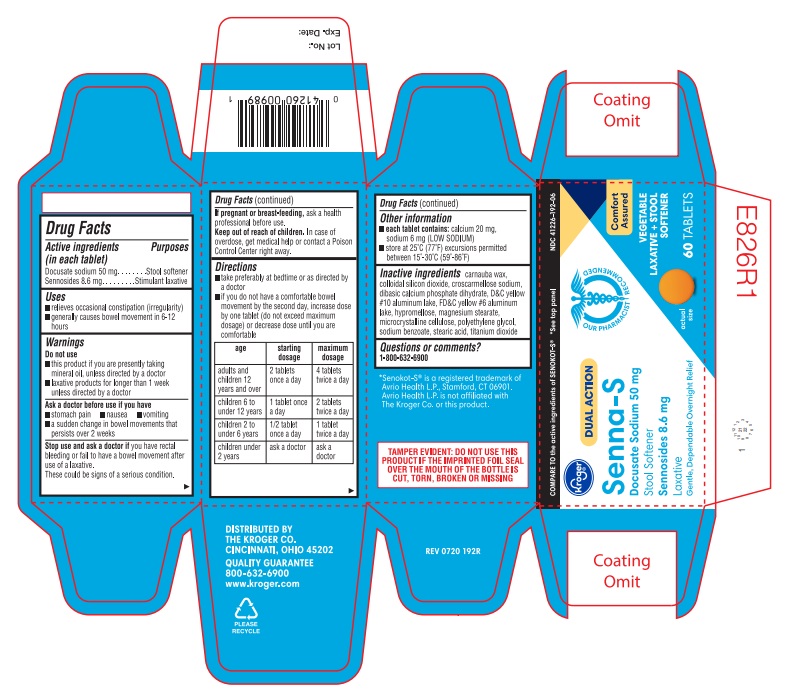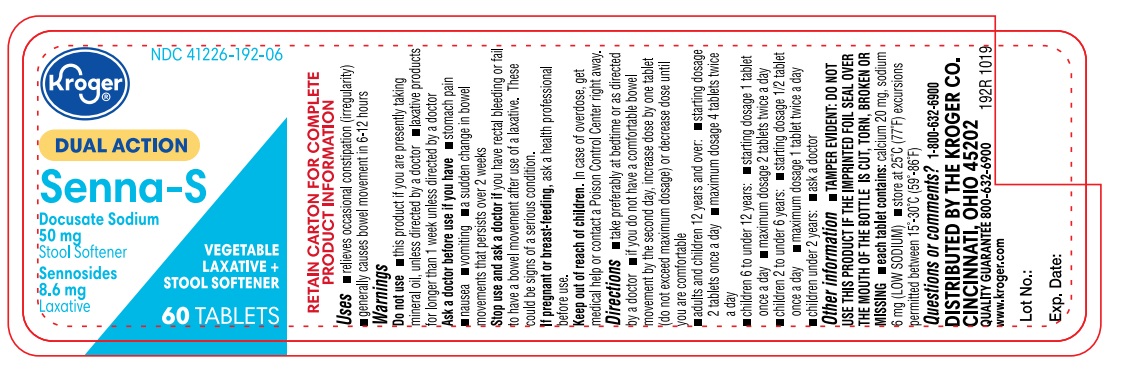 DRUG LABEL: SENNA-S
NDC: 41226-192 | Form: TABLET, COATED
Manufacturer: KROGER
Category: otc | Type: HUMAN OTC DRUG LABEL
Date: 20250210

ACTIVE INGREDIENTS: SENNOSIDES 8.6 mg/1 1; DOCUSATE SODIUM 50 mg/1 1
INACTIVE INGREDIENTS: TITANIUM DIOXIDE; MAGNESIUM STEARATE; HYPROMELLOSES; MICROCRYSTALLINE CELLULOSE; STEARIC ACID; SODIUM BENZOATE; DIBASIC CALCIUM PHOSPHATE DIHYDRATE; FD&C YELLOW NO. 6 ALUMINUM LAKE; CROSCARMELLOSE SODIUM; D&C YELLOW NO. 10 ALUMINUM LAKE; CARNAUBA WAX; SILICON DIOXIDE; POLYETHYLENE GLYCOL, UNSPECIFIED

KROGER 41226-192-06 (SENNA-S)

Active ingredients (in each tablet)

Docustate sodium 50 mg

Sennosides 8.6 mg

Purposes

Stool softner

Laxative

Uses

- Relieves occasional constipation (irregularity)
- generally causes bowel movement in 6-12 hours

Warnings

Do not use

- if you are now taking mineral oil, unless directed by a doctor
- laxative products for longer than 1 week unless directed by a doctor

Ask a doctor before use if you have

- stomach pain
- nausea
- vomiting
- noticed a sudden change in bowel habits that continues over a period of 2 weeks

Stop use and ask a doctor if you have rectal bleeding or fail to have a bowel movement after use of a laxative. These may indicate a serious condition.

PREGNANCY OR BREAST FEEDING

If pregnant or breast-feeding, ask a health professional before use.

Keep out of reach of children. In case of overdose, get medical help or contact a Poison Control Center right away (1-800-222-1222).

Directions

- take preferably at bedtime or as directed by a doctor

age | starting dosage | maximum dosage
adults and children 12 years of age and over | 2 tablets once a day | 4 tablets twice a day
children 6 to under 12; years | 1 tablet once a day | 2 tablets twice a day
children 2 to under 6; years | ½ tablet once a day | 1 tablet twice a day
children under 2 years | ask a doctor | ask a doctor

Other information

- each tablet contains: calcium 20 mg, sodium 6 mg (LOW SODIUM)
- store at 25°C (77°F) excursions permitted between 15°-30°C (59°-86°F)

INACTIVE INGREDIENT

Inactive ingredientscarnauba wax, colloidal silicon dioxide, croscarmellose sodium, dibasic calcium phosphate dihydrate, D&C yellow #10 aluminum lake, FD&C yellow #6 aluminum lake, hypromellose, magnesium stearate, microcrystalline cellulose, polyethylene glycol, sodium benzoate, stearic acid, titanium dioxide

Questions or comments? Call 1-877-290-4008